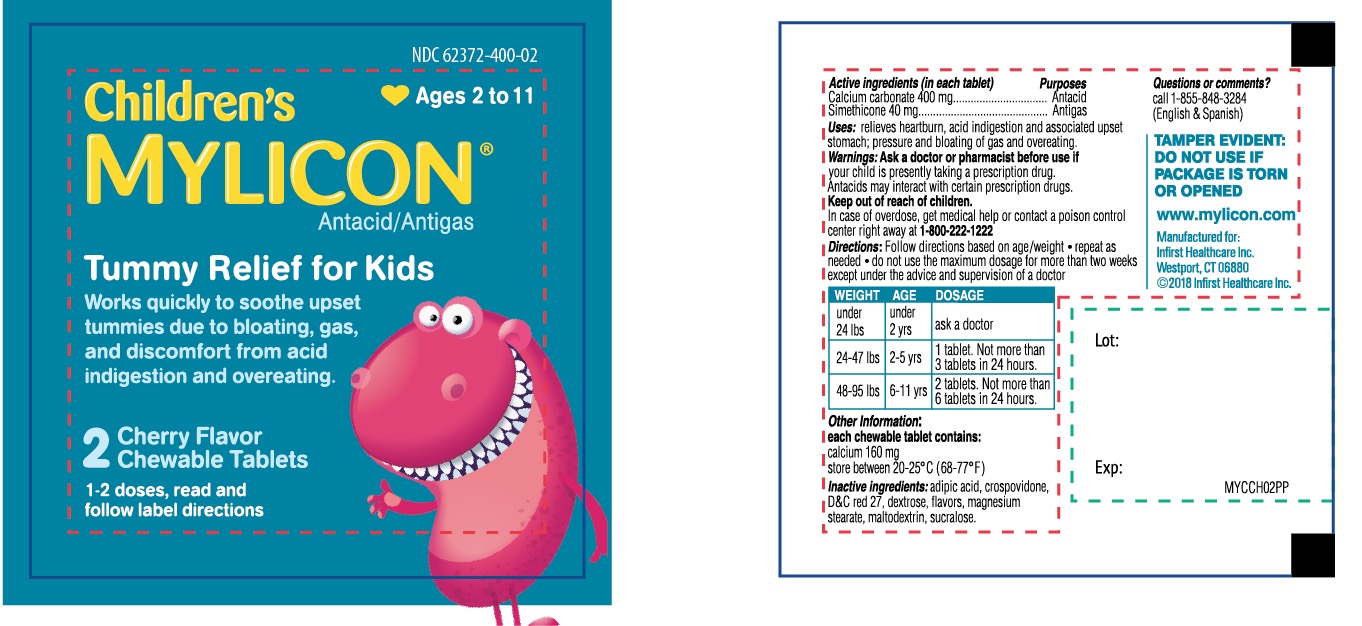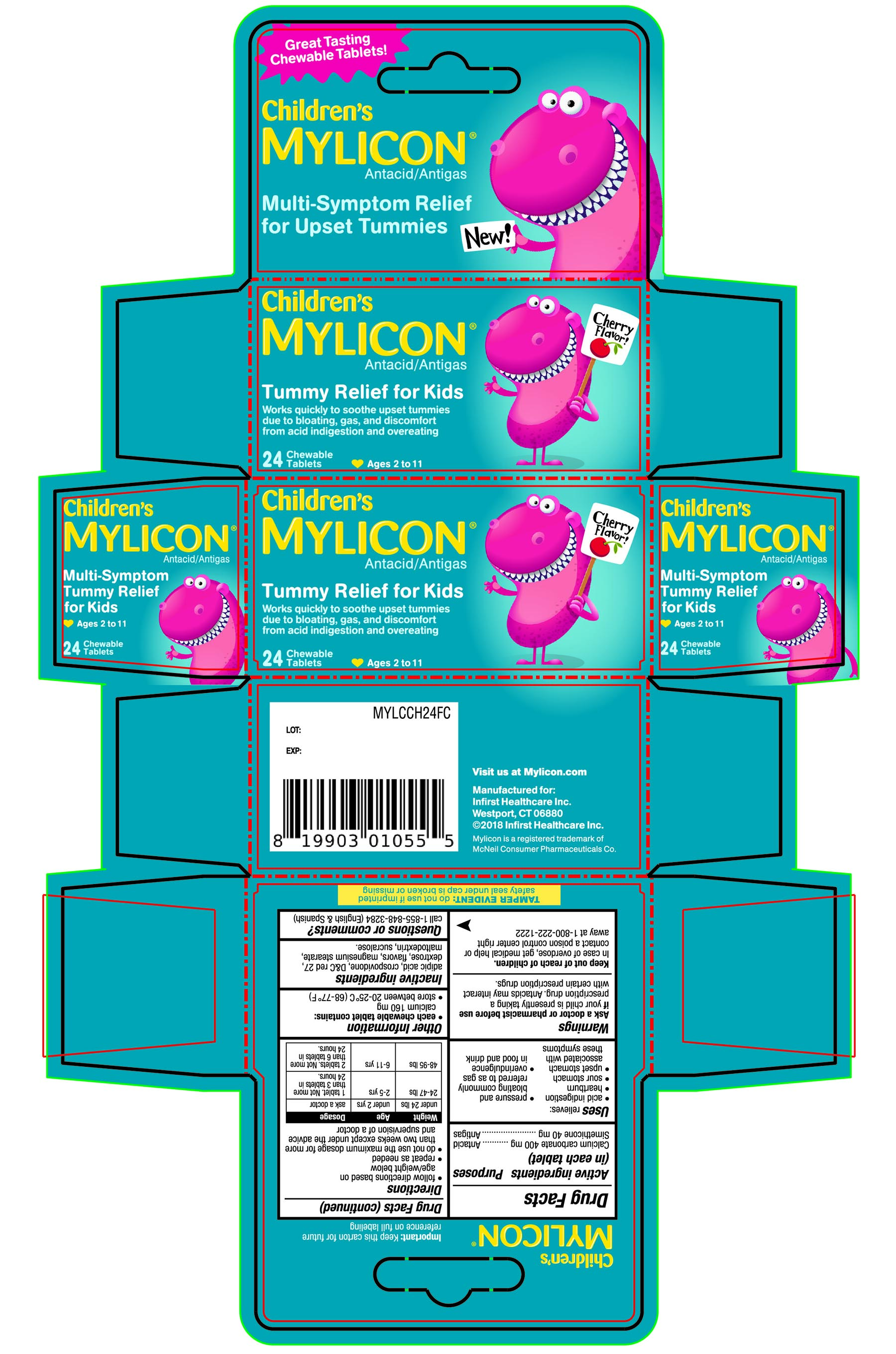 DRUG LABEL: Childrens Mylicon Tummy Relief for Kids
NDC: 62372-400 | Form: TABLET, CHEWABLE
Manufacturer: Infirst Healthcare Inc.
Category: otc | Type: HUMAN OTC DRUG LABEL
Date: 20231201

ACTIVE INGREDIENTS: CALCIUM CARBONATE 400 mg/1 1; DIMETHICONE 40 mg/1 1
INACTIVE INGREDIENTS: ADIPIC ACID; CROSPOVIDONE (15 MPA.S AT 5%); D&C RED NO. 27; DEXTROSE, UNSPECIFIED FORM; MAGNESIUM STEARATE; MALTODEXTRIN; SUCRALOSE

Children’s Mylicon Tummy Relief for Kids

Active ingredients (in each tablet)

Calcium carbonate 400 mg

Simethicone 40 mg

Purposes

Antacid

Antigas

Uses

relieves:

- acid indigestion
- heartburn
- sour stomach
- upset stomach associated with these symptoms
- pressure and bloating commonly referred to as gas
- overindulgence in food and drink

Warnings

Ask a doctor or pharmacist before use if

your child is presently taking a prescription drug. Antacids may interact with certain prescription drugs.

Keep out of reach of children.

In case of overdose, get medical help or contact a poison control center right away at 1-800-222-1222

Directions

- follow directions based on age/weight below
- repeat as needed
- do not use the maximum dosage for more than two weeks except under the advice and supervision of a doctor

Weight | Age | Dosage
under 24 lbs | under 2 yrs | ask a doctor
24-47 lbs | 2-5 yrs | 1 tablet, Not more than 3 tablets in 24 hours
48-95 lbs | 6-11 yrs | 2 tablets, Not more than 6 tablets in 24 hours

Other information

- e ach chewable tablet contains:calcium 160 mg
- store between 20-25°C (68-77°F)

Inactive ingredients

adipic acid, crospovidone, D&C red 27, dextrose, flavors, magnesium stearate, maltodextrin, sucralose,

Questions or comments?

call 1-855-848-3284 (English & Spanish)

Package/Label Principal Display Panel

Great tasting Chewable Tablets!

- New!

Children’s MYLICON®Antacid/ Antigas

Tummy Relief for Kids

Works quickly to soothe upset tummies

due to bloating, gas and discomfort

from acid indigestion and overeating

- Multi- Symptom Relief for Upset Tummies
- Multi-Symptom Tummy Relief for Kids

Cherry Flavor!

24 CHEWABLE TABLETS Ages 2 to 11

Important: Keep this carton for future reference on full labeling.

Visit us at Mylicon.com

Manufactured for:

Infirst Healthcare Inc,

Westport, CT 06880

©2018 Infirst Healthcare Inc.

Mylicon is a registered trademark of McNeil Consumer Pharmaceuticals Co,

TAMPER EVIDENT: do not use if imprinted safety seal under cap is broken or missing.